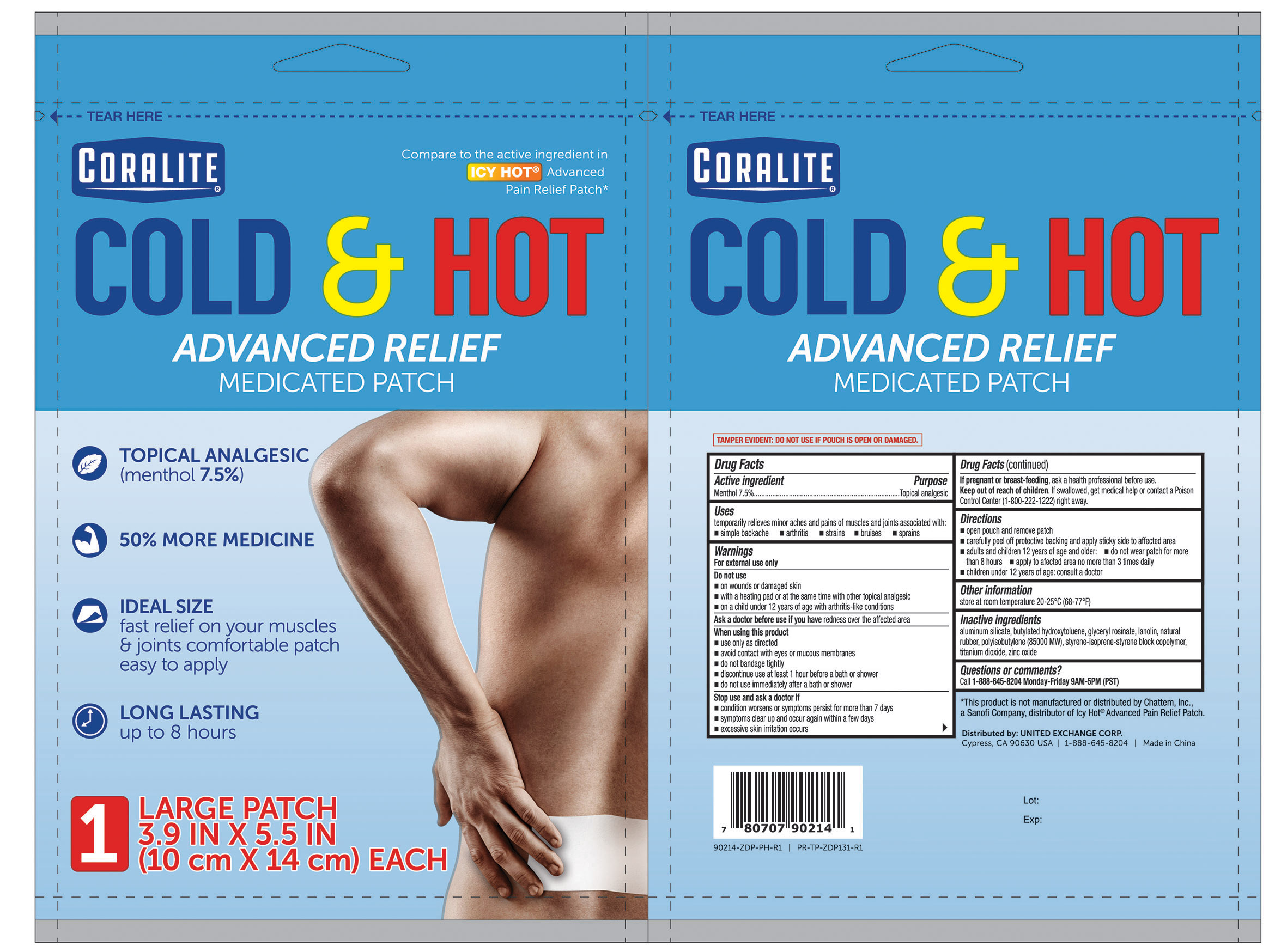 DRUG LABEL: Coralite Cold and Hot
NDC: 65923-214 | Form: PATCH
Manufacturer: United Exchange Corp.
Category: otc | Type: HUMAN OTC DRUG LABEL
Date: 20251022

ACTIVE INGREDIENTS: MENTHOL 210 mg/1 1
INACTIVE INGREDIENTS: STYRENE/ISOPRENE/STYRENE BLOCK COPOLYMER; LANOLIN; GLYCERYL ROSINATE; NATURAL LATEX RUBBER; BUTYLATED HYDROXYTOLUENE; TITANIUM DIOXIDE; ZINC OXIDE; POLYISOBUTYLENE (85000 MW); ALUMINUM SILICATE

Coralite Cold & Hot Advanced Relief Medicated Patch 7.5 Menthol 1ct 90214

Active ingredient Purpose

Menthol 7.5%...............................................................Topical analgesic

Uses

temporarily relieves minor aches and pains of muscles and joints associated with:

- simple backache
- arthritis
- strains
- bruises
- sprains

Warnings

For external use only

Do not use

- on wounds or damaged skin
- with a heating pad or at the same time with other topical analgesic
- on a child under 12 years of age with arthritis-like conditions

Ask a doctor before use if you have redness over the affected area

When using this product

- use only as directed
- avoid contact with eyes or mucous membranes
- do not bandage tightly
- discontinue use at least 1 hour before a bath or shower
- do not use immediately after a bath or shower

Stop use and ask a doctor if

- conditions worsens or symptoms persist for more than 7 days
- symptoms clear up and occur again within a few days
- excessive skin irritation occurs

PREGNANCY OR BREAST FEEDING

If pregnant or breast-feeding, ask a health professional before use.

Keep out of reach of children. If swallowed, get medical help or contact a Poison Control Center (1-800-222-1222) right away.

Directions

- open pouch and remove patch
- carefully peel off protective backing and apply sticky side to affected area
- adults and children 12 years of age and older:
- do not wear patch for more than 8 hours
- apply to affected area no more than 3 times daily
- children under 12 years of age: consult a doctor

Other information

store at room temperature 20-25°C (68-77°F)

Inactive ingredients

aluminum silicate, butylated hydroxytoluene, glyceryl rosinate, lanolin, natural rubber, polyisobutylene (85000 MW), styrene-isoprene-styrene block copolymer, titanium dioxide, zinc oxide

DOSAGE AND ADMINISTRATION

Distributed by:

UNITED EXCHANGE CORP.

Cypress, CA 90630 USA

Made in China